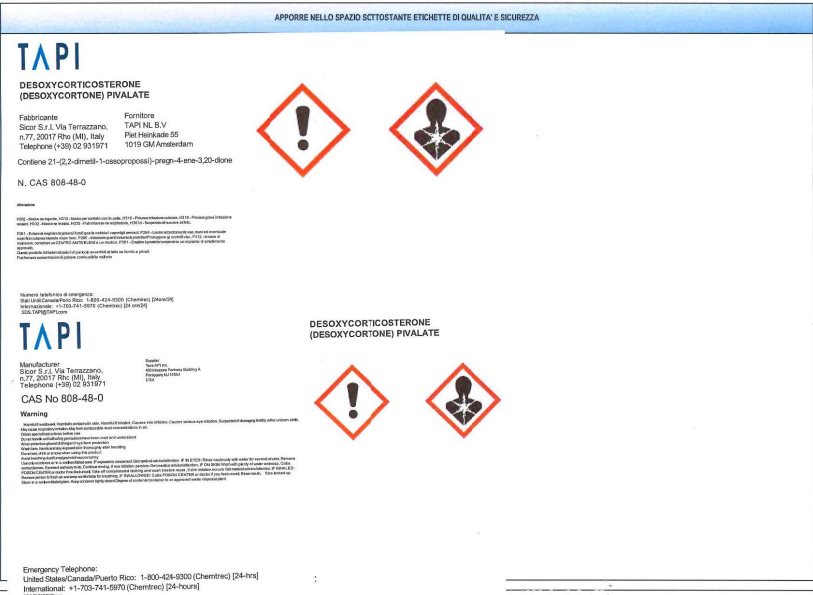 DRUG LABEL: Desoxycorticosterone Pivalate
NDC: 58198-6450 | Form: POWDER, FOR SUSPENSION
Manufacturer: Elanco US Inc.
Category: other | Type: BULK INGREDIENT - ANIMAL DRUG
Date: 20260115

ACTIVE INGREDIENTS: DESOXYCORTICOSTERONE PIVALATE 15 kg/15 kg

Desoxycorticosterone Pivalate